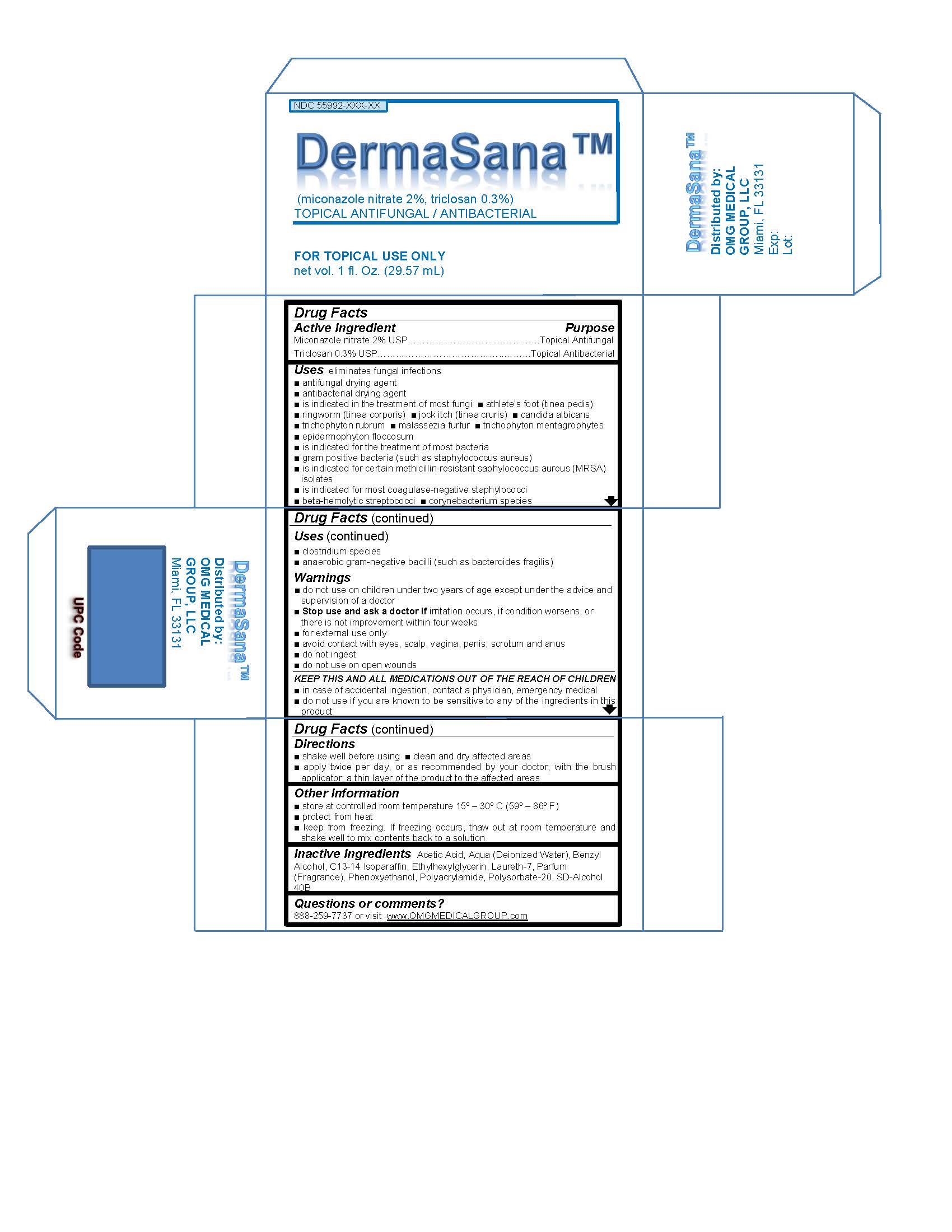 DRUG LABEL: DermaSana
NDC: 55992-023 | Form: CREAM
Manufacturer: OMG Medical Group, LLC
Category: otc | Type: HUMAN OTC DRUG LABEL
Date: 20130301

ACTIVE INGREDIENTS: MICONAZOLE NITRATE 200 mg/1 mg; TRICLOSAN 30 mg/1 mg
INACTIVE INGREDIENTS: ACETIC ACID; WATER; BENZYL ALCOHOL; C13-14 ISOPARAFFIN; ETHYLHEXYLGLYCERIN; LAURETH-7; PHENOXYETHANOL; POLYACRYLAMIDE (10000 MW); POLYSORBATE 20; ALCOHOL

DermaSana

Warnings

do not used on children under two years of age except under the advice and supervision of a doctor

stop use and ask a doctor if irritation occurs, if conditions worsens, or there is not improvement within four weeks.

for external use only

avoid contact with eyes, scalp, vagina, penis, scrotum and anus

do not ingest

do not use on open wounds

in case of accidental ingestion contact a physician, emergency medical

do not use if you are known to be sensitive to any of the ingredients in this product

active ingredient

miconazole nitrate 2% USP

triclosan 0.3% USP

purpose

topical antifungal

topical antibacterial

KEEP OUT OF REACH OF CHILDREN

Keep this and all medications our of the reach of children

directions

shake well before using

clean and dry affected areas

apply twice per day or as recommended by your doctor

with the brush applicator a thin layer of the product to the affected areas

uses

antifungal drying agent

antibacterial drying agent

is indicated in the treatment of most fungi

athlete's foot (tinea pedis)

ringworm (tinea corporis)

jock itch (tinea cruris)

candida albicans

trichophyton rubrum

malassezia furfur

trichophyton mentagrophytes

epidemophyton floccsum

is indicated for the treatment of most bacteria

gram positive bacteria (such as staphyloocccous aureus)

is indicated for certain methicillin resistant saphylococcus aureus (MRSA) isolates

is indicated for most coagulase-negative staphylococci

beta hemolytic streptococci

corynebacterium species

clostridium species

anaerobic gram-negative bacilli (such as bacteriodes fragilis)

other information

store at controlled room temperature 15-30 degrees celcius (59-86 degrees farenhight)

protect from heat

keep from freezing, if freezing occurs, thaw out at room temperature and shake well to mix contents back to a solution

INACTIVE INGREDIENT

acetic acid, aqua (deionized water), benzyl alcohol, c13-14 isoparaffin, ethylhexylglycerin, laureth 7, parfum, phenoxyethanol, polyacrylamide, polysorbate 20, sd-alcohol 40B